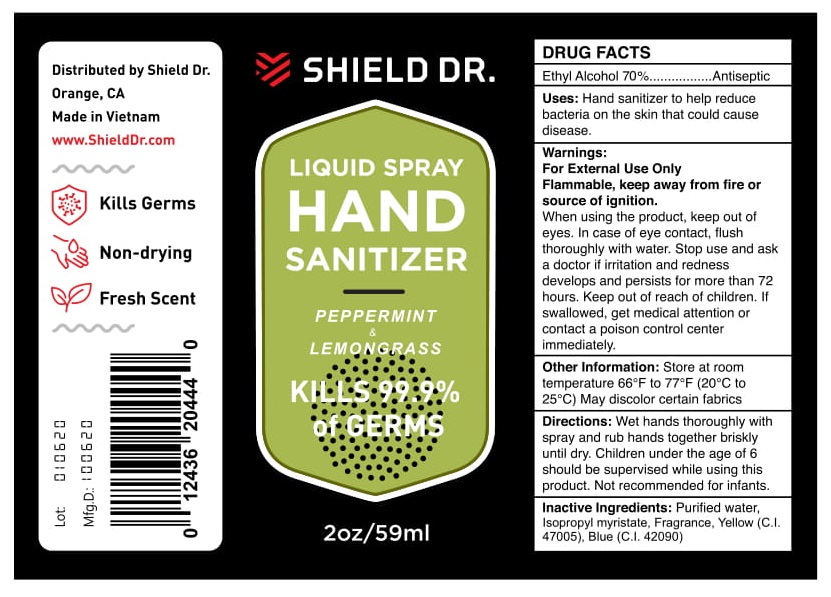 DRUG LABEL: Shield Dr.
NDC: 79633-302 | Form: LIQUID
Manufacturer: MEDIPHARCO PHARMACEUTICAL JOINT STOCK COMPANY
Category: otc | Type: HUMAN OTC DRUG LABEL
Date: 20200819

ACTIVE INGREDIENTS: ALCOHOL 70 mL/100 mL
INACTIVE INGREDIENTS: POLYOXYL 40 HYDROGENATED CASTOR OIL; WATER; ISOPROPYL MYRISTATE; JAMMU LEMONGRASS OIL; D&C YELLOW NO. 10; FD&C BLUE NO. 1; PEPPERMINT OIL

ACTIVE INGREDIENT

Ethyl Alcohol 70%

INACTIVE INGREDIENT

Purified water, Isopropyl myristate, Fragrance, Yello (C.I. 47005), Blue (C.I. 42090)

KEEP OUT OF REACH OF CHILDREN

If swallowed, get medical attention or contact poison control center immediately

WARNINGS

For external use only.

Flammable, keep away from fire or source of ignition.

INDICATIONS AND USAGE

Hand sanitizer to help reduce bacteria on the skin it could cause disease

DOSAGE AND ADMINISTRATION

Wet hand thoroughly with spray and rub hand together briskly until dry. Children under the age of 6 should be supervised while using this product. Not recommended for infants.

PURPOSE

Antiseptic

STORAGE AND HANDLING

Store at room temperature 66o F to 77oF (20oC to 25oC)

PACKAGE LABEL

59ml NDC: 79633-302-59